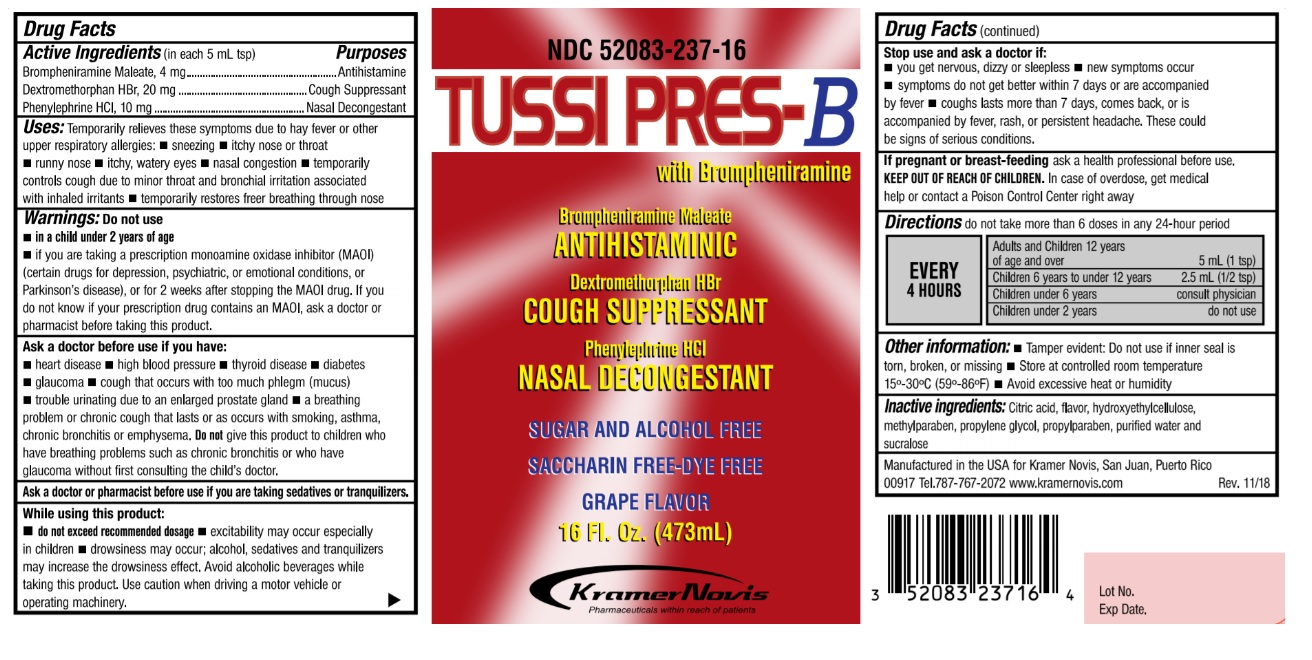 DRUG LABEL: Tussi Pres B
NDC: 52083-237 | Form: SYRUP
Manufacturer: KRAMER NOVIS
Category: otc | Type: HUMAN OTC DRUG LABEL
Date: 20251114

ACTIVE INGREDIENTS: DEXTROMETHORPHAN HYDROBROMIDE 20 mg/5 mL; BROMPHENIRAMINE MALEATE 4 mg/5 mL; PHENYLEPHRINE HYDROCHLORIDE 10 mg/5 mL
INACTIVE INGREDIENTS: CITRIC ACID MONOHYDRATE; HYDROXYETHYL CELLULOSE (1500 MPA.S AT 1%); METHYLPARABEN; PROPYLENE GLYCOL; PROPYLPARABEN; WATER; SUCRALOSE

TUSSI PRES- B

Active Ingredients (in each 5 mL tsp)

Brompheniramine Maleate, 4 mg

Dextromethorphan HBr, 20 mg

Phenylephrine HCl, 10 mg

Purposes

Antihistamine

Cough Suppressant

Nasal Decongestant

INDICATIONS AND USAGE

Uses: Temporarily relieves these symptoms due to hay fever or other upper respiratory allergies: • sneezing • itchy nose or throat • runny nose • itchy, watery eyes • nasal congestion • temporarily controls cough due to minor throat and bronchial irritation associated with inhaled irritants • temporarily restores freer breathing through nose.

Warnings: Do not use

• in a child under 2 years of age

• if you are now taking a prescription monoamine oxidase inhibitor (MAOI) (certain drugs for depression, psychiatric, or emotional conditions, or Parkinson's disease), or for 2 weeks after stopping MAOI drug. If you do not know if your prescription drug contains an MAOI, ask a doctor or pharmacist before taking this product.

Ask a doctor before use if you have:

• heart disease • high blood pressure • thyroid disease • diabetes • glaucoma • cough that occurs with too much phlegm (mucus) • trouble urinating due to an enlarged prostate gland • a breathing problem or chronic cough that lasts or as occurs with smoking, asthma, chronic bronchitis or emphysema. Do not give this product to children who have breathing problems such as chronic bronchitis or who have glaucoma without first consulting the child's doctor.

Ask a doctor or pharmacist before use if you are taking sedatives or tranquilizers.

While using this product:

• do not exceed recommended dosage • excitability may occur especially in children • drowsiness may occur; alcohol, sedatives and tranquilizers may increase the drowsiness effect. Avoid alcoholic beverages while taking this product. Use caution when driving a motor vehicle or operating machinery.

Stop use and ask a doctor if:

• if you get nervous, dizzy or sleepless • new symptoms occur • symptoms do not get better within 7 days or are accompanied by fever • cough lasts more than 7 days, comes back, or is accompanied by fever, rash or persistent headache. These could be signs of serious conditions.

If pregnant or breast-feeding ask a health professional before use.

KEEP OUT OF REACH OF CHILDREN. In case of overdose, get medical help or contact a Poison Control Center right away.

DOSAGE AND ADMINISTRATION

Directions do not take more than 6 doses in any 24-hour period

EVERY 4 HOURS | Adults and Children 12 years of age and over 5mL (1tsp)
EVERY 4 HOURS | Children 6 years to under 12 years 2.5mL (1/2 tsp)
EVERY 4 HOURS | Children under 6 years consult physician
EVERY 4 HOURS | Children under 2 years do not use

Other information: • Tamper evident: Do not use if inner seal is torn, broken or missing • Store at controlled room temperature 15°-30°C (59°-86°F) • Avoid excess heat or humidity

INACTIVE INGREDIENT

Inactive ingredients: Citric acid, flavor, hydroxyethylcellulose, methylparaben, propylene glycol, propylparaben, purified water and sucralose

Brompheniramine Maleate
ANTIHISTAMINE

Dextromethorphan HBr
COUGH SUPPRESSANT

Phenylephrine HCl
NASAL DECONGESTANT

SUGAR AND ALCOHOL FREE

SACCHARIN FREE

DYE FREE

GRAPE FLAVOR

Manufactured in the USA for Kramer Novis, San Juan, Puerto Rico 00917 Tel.787-767-2072 www.kramernovis.com